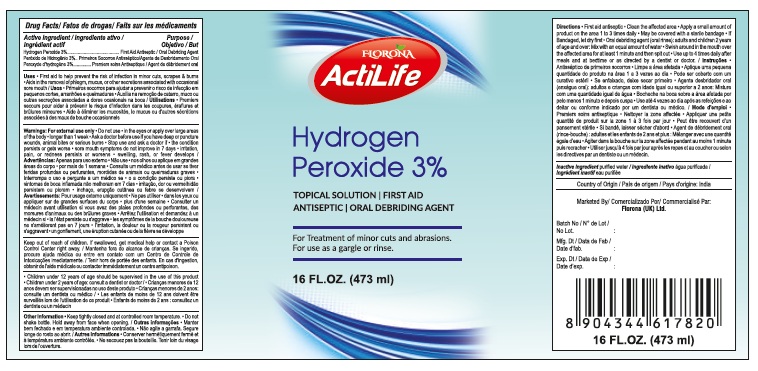 DRUG LABEL: FLORONA ACTILIFE HYDROGEN PEROXIDE 3 %
NDC: 85891-006 | Form: LIQUID
Manufacturer: SPARROW LIFE CARE PRIVATE LIMITED
Category: otc | Type: HUMAN OTC DRUG LABEL
Date: 20250721

ACTIVE INGREDIENTS: HYDROGEN PEROXIDE 3 mL/100 mL
INACTIVE INGREDIENTS: WATER

Active Ingredient

Hydrogen peroxide 3%

Purpose

First Aid Antiseptic

Uses

First aid to help prevent the risk of infection in
• Minor cuts
• Scrapes
• Burns
• Aids in the removal of phlegm, Mucus, or other secretions associated with occasional sore mouth.

Warnings

- For external use only
- Do not use
- in the eyes or apply over large area of the body Longer 1 week
- Ask doctor before use if you have deep or puncture wounds, animal bites or serious burns.
- Stop use and ask a doctor if the condition persist or gets worse
- Sore mouth symptoms do not improve in 7 days
- irritation, pain, or redness persist or worsen
- swelling, rash or Fever develops
- Keep out of reach of children :If swallowed ,get medical help or contact a Poison Control Center right away .
- Children under 12 years of age should be supervised in the use of this product
- Children under 2 year of age : consult a dentist or doctor.

Directions

- First aid antiseptic
- Clean the affected area
- Apply a small amount of product on the area 1 to 3 times daily
- May be covered with a sterile bandage
- If bandage, let dry first
- Oral debriding agent (oral rinse): adults and children 2 years of age and over: Mix with an equal amount of water
- Swish around in the mouth over the affected area for atleast 1 minute and then spit out.
- Use up to 4 times daily after meals and after bedtime or as direacted by a dentist or doctor

Other Information

- Keep bottle tightly closed and controlled room temperature.
- Do not shake bottle. Hold away from face when opening.

Inactive ingredients

Water